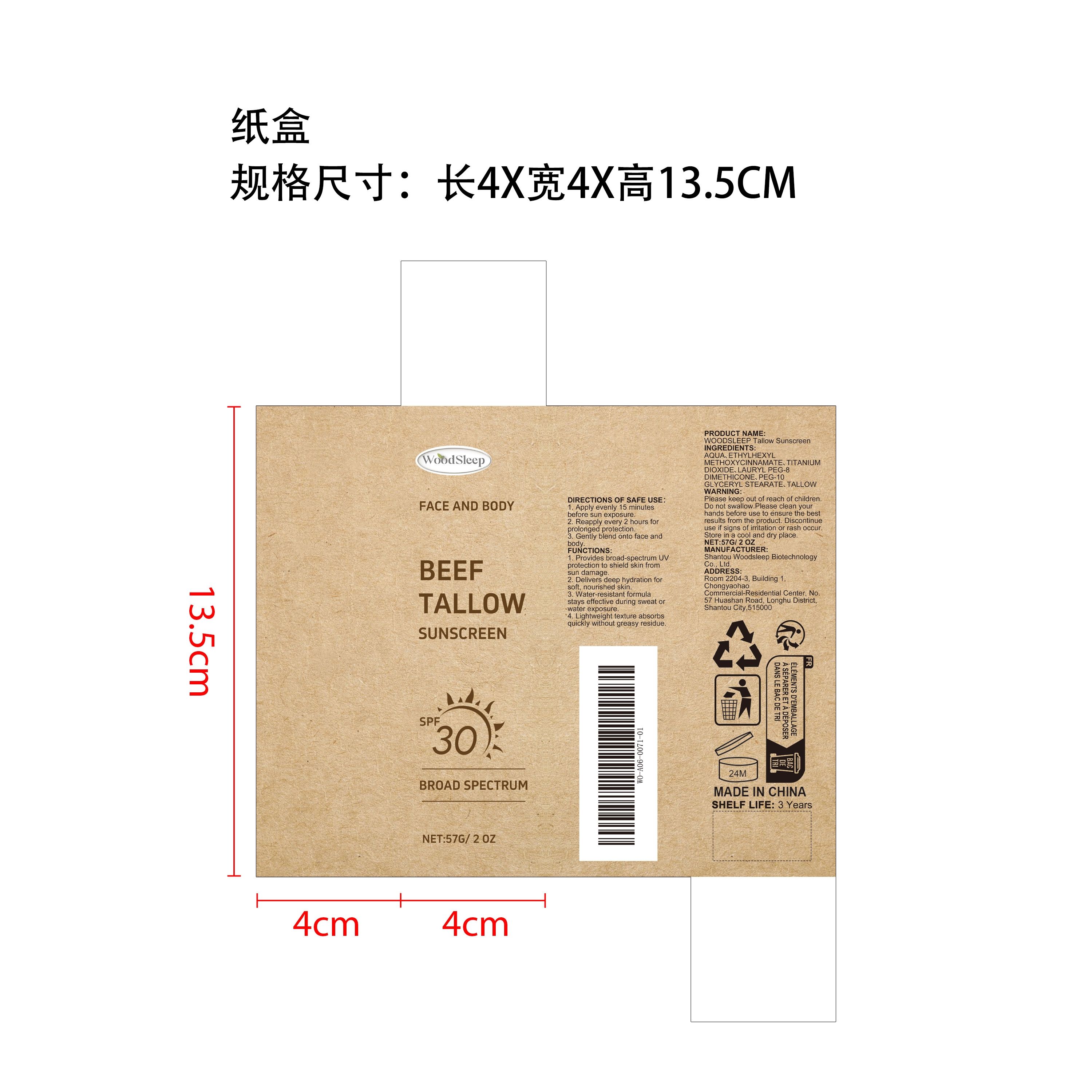 DRUG LABEL: WOODSLEEP Tallow Sunscreen
NDC: 85053-002 | Form: CREAM
Manufacturer: Shantou Woodsleep Biotechnology Co., Ltd.
Category: otc | Type: HUMAN OTC DRUG LABEL
Date: 20251126

ACTIVE INGREDIENTS: TALLOW 0.0114 mg/57 mg
INACTIVE INGREDIENTS: PEG-10 GLYCERYL STEARATE 0.57 mg/57 mg; TITANIUM DIOXIDE 1.14 mg/57 mg; AQUA 50.7186 mg/57 mg; LAURYL PEG-8 DIMETHICONE (300 CPS) 3.42 mg/57 mg; ETHYLHEXYL METHOXYCINNAMATE 1.14 mg/57 mg

ACTIVE INGREDIENT

TALLOW

WHEN USING

Apply evenly 15 minutes before sun exposure.
Reapply every 2 hours for prolonged protection.

Gently blend onto face and body.

PURPOSE

Sunscreen barrier: fully blocks UV rays and protects skin health.
Deep moisturizing: prevents dryness and keeps skin moisturized.
Sports adaptability: swimming and fitness without makeup removal, more lasting protection.
Lightweight and comfortable: silky and fits the skin, no burden to the touch.
Suitable for daily commuting, can be used alone or as a primer before makeup.
Mild formula reduces irritation, sensitive skin friendly.
Improves skin smoothness and soft touch.
Light texture, does not clog pores.
Suitable for a variety of skin types and skin tones, easy to control.
Re-application does not rub mud, convenient and not embarrassing.
Balance the water and oil status of the skin to avoid drying.
Reduce the loss of protective power caused by the external environment.
Natural nude makeup effect, no fake face and no oily shine.
Portable packaging design, worry-free re-application anytime, anywhere.
Strengthen the skin's ability to resist daily environmental pressure.

DO NOT USE

Discontinue use if signs of irritation or rash occur.

STOP USE

Discontinue use if signs of irritation or rash occur.

KEEP OUT OF REACH OF CHILDREN

Please keep out of reach of children. Do not swallow.

WARNINGS

Please keep out of reach of children. Do not swallow.Please clean your hands before use to ensure the best results from the product. Discontinue use if signs of irritation or rash occur. Store in a cool and dry place.

INACTIVE INGREDIENT

AQUA、LAURYL PEG-8 DIMETHICONE、ETHYLHEXYL METHOXYCINNAMATE、TITANIUM DIOXIDE、PEG-10 GLYCERYL STEARATE

STORAGE AND HANDLING

Store in a cool and dry place.